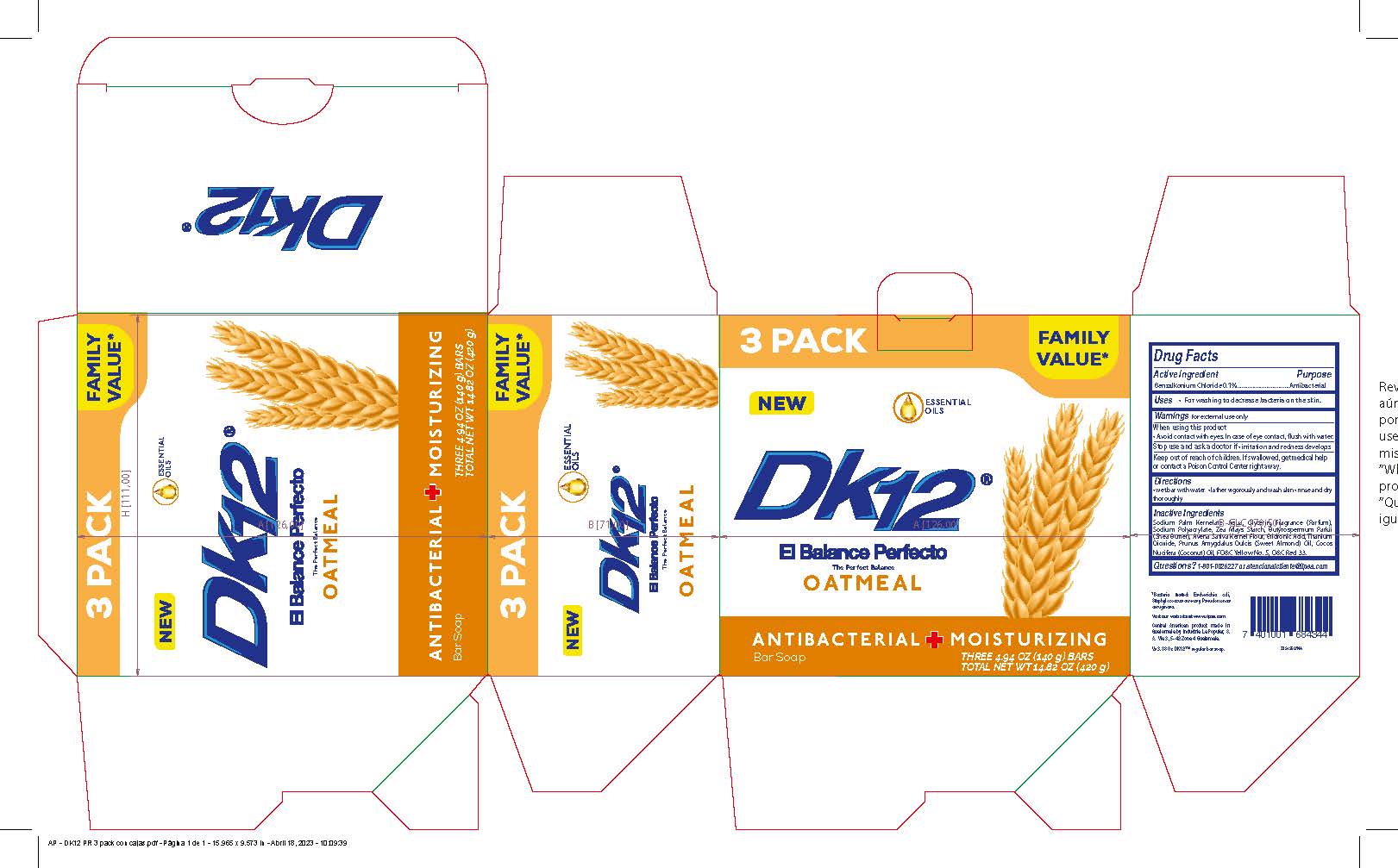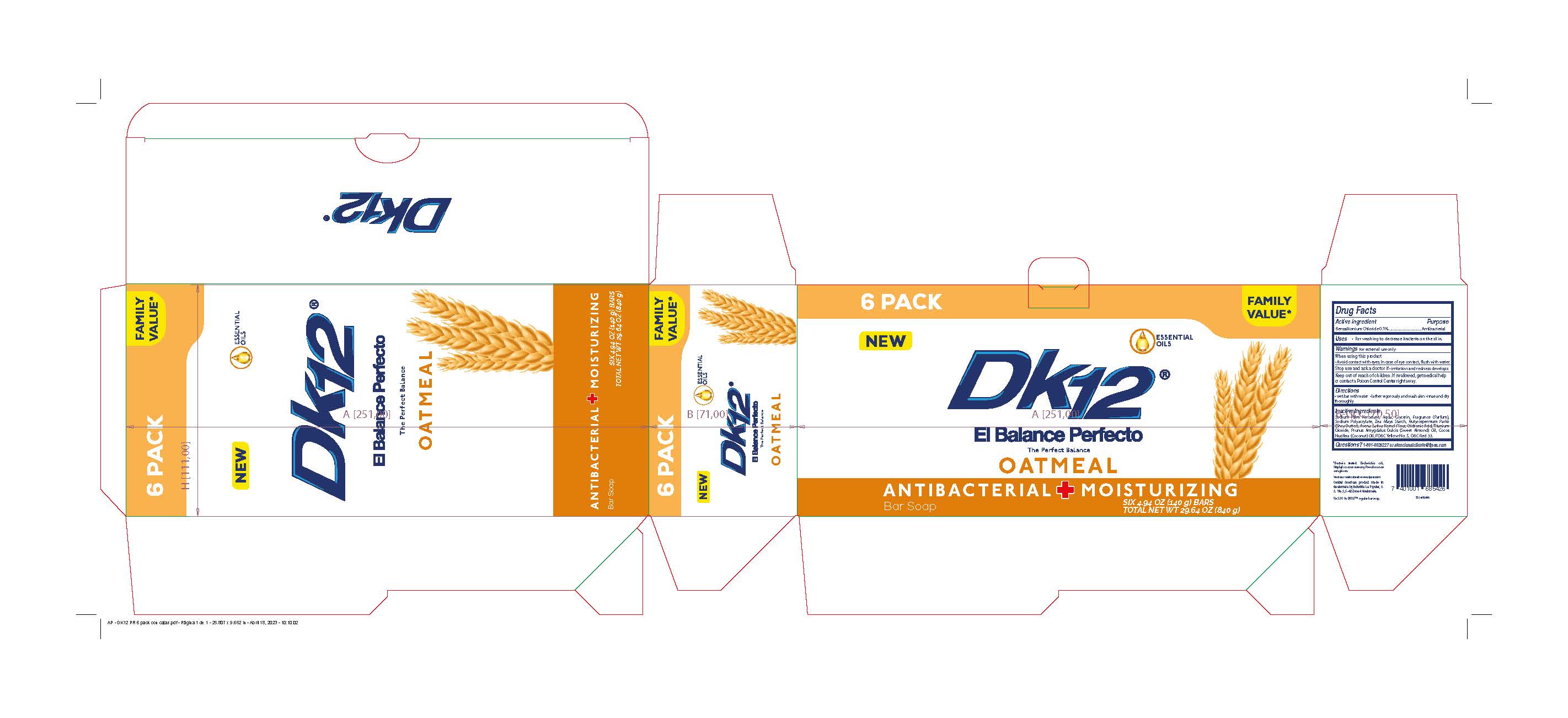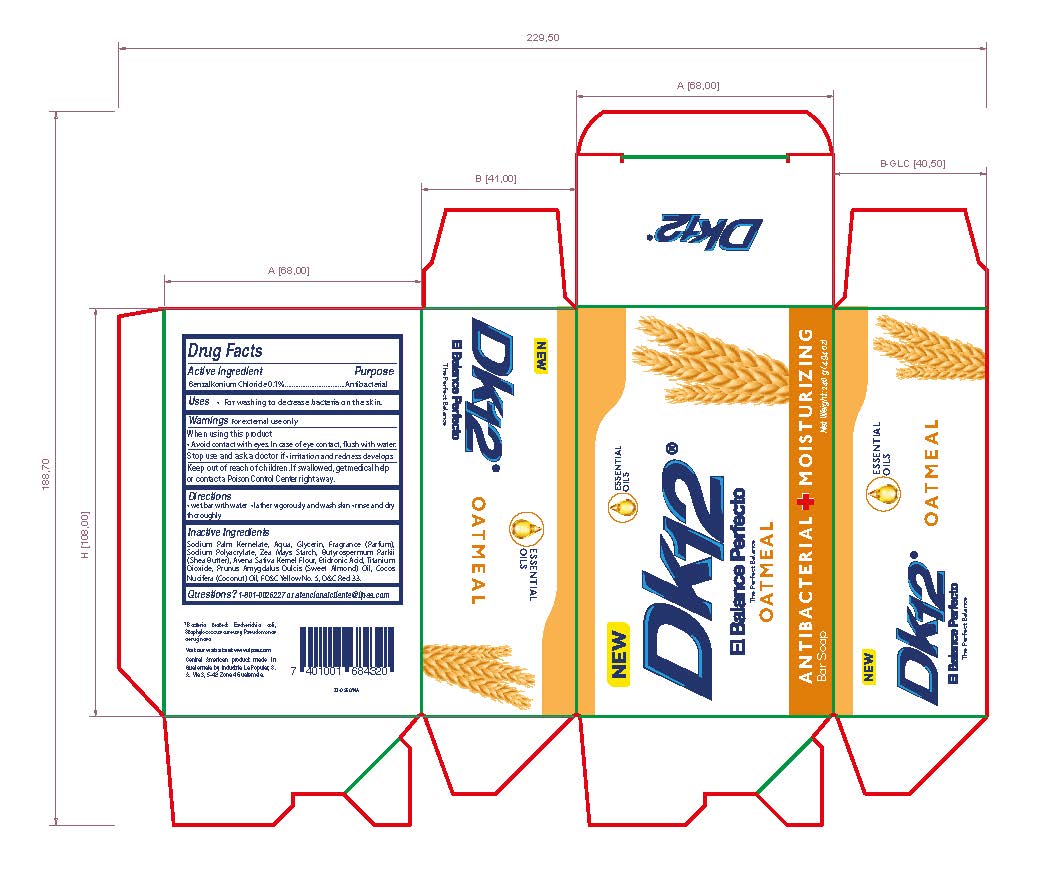 DRUG LABEL: DK12 Oatmeal Antibacterial and Moisturizing
NDC: 62476-104 | Form: SOAP
Manufacturer: Industria La Popular, S.A.
Category: otc | Type: HUMAN OTC DRUG LABEL
Date: 20241202

ACTIVE INGREDIENTS: BENZALKONIUM CHLORIDE 0.1 g/110 g
INACTIVE INGREDIENTS: D&C RED NO. 33; PRUNUS DULCIS BARK; OATMEAL; SODIUM PALM KERNELATE; GLYCERIN; WATER; TITANIUM DIOXIDE; SODIUM POLYACRYLATE (8000 MW); ETIDRONIC ACID; STARCH, CORN; BUTYROSPERMUM PARKII (SHEA) BUTTER UNSAPONIFIABLES; COCONUT OIL; FD&C YELLOW NO. 5

DK12 Oatmeal Bar Soap Antibacterial and Moisturizing

Active Ingredient

Benzalkonium Chloride 0.1%

Purpose

Antibacterial

Uses

For washing to decrease bacteria on the skin.

Warnings

For External Use only.

When using this product

Avoid contact with eyes. In case of eye contact, flush with water.

Stop use and ask a doctor

If irritation and redness develops

Keep out of reach of children.

If swallowed, get medical help or contact a Poison Control Center right away.

Directions

Wet bar with water
Lather vigorously and wash skin

Rinse and dry thoroughly

Inactive Ingredients

Sodium Palm Kernelate, Water, Glycerin, Fragrance (Perfume), Sodium Polyacrylate, Zea May Starch, Butyrospermum Parkii (Shea Butter), Oatmeal Sativa Kernel Flour, Etidronic Acid, Titanium Dioxide, Prunus Amygdalus Dulcis (Sweet Almond) Oil, Cocos Nucitera (coconut) oil, FD&C Yellow No.5, D&C Red No. 33

Questions

1-801-0026227 or atencionalcliente@ilpsa.com